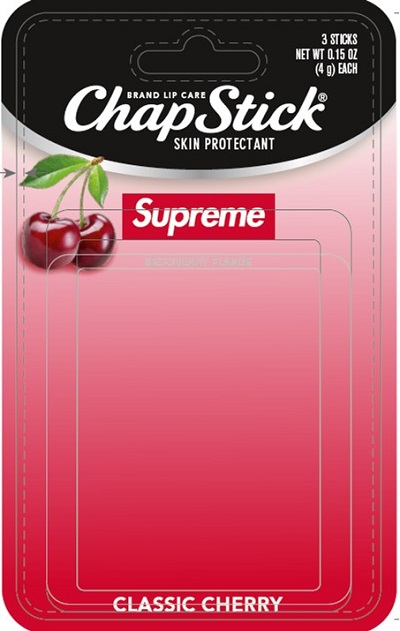 DRUG LABEL: ChapStick Supreme Classic Cherry
NDC: 0573-1921 | Form: STICK
Manufacturer: Haleon US Holdings LLC
Category: otc | Type: HUMAN OTC DRUG LABEL
Date: 20240322

ACTIVE INGREDIENTS: PETROLATUM 450 mg/1 g
INACTIVE INGREDIENTS: ARACHIDYL PROPIONATE; CAMPHOR (NATURAL); CARNAUBA WAX; CETYL ALCOHOL; ISOPROPYL MYRISTATE; LANOLIN; LIGHT MINERAL OIL; MENTHOL, UNSPECIFIED FORM; OCTYLDODECANOL; PARAFFIN; PHENYL TRIMETHICONE; D&C RED NO. 6; SACCHARIN; WHITE WAX

Drug Facts

Active ingredient

White Petrolatum 45%

Purpose

Skin Protectant

Uses

- helps prevent and temporarily protects chafed, chapped or cracked lips
- helps prevent and protect from the drying effects of wind and cold weather

Warnings

For external use only

Keep out of reach of children. If swallowed, get medical help or contact a Poison Control Center right away.

Directions

apply as needed

Other Information

store at 20-25°C (68-77°F)

Inactive ingredients

arachidyl propionate, camphor, carnauba wax, cetyl alcohol, fragrance, isopropyl lanolate, isopropyl myristate, lanolin, light mineral oil, menthol, octyldodecanol, paraffin, phenyl trimethicone, red 6 lake, saccharin, white wax

Questions or Comments?

Call weekdays from 9 AM to 6 PM EST at 1-800-245-1040

Additional information

Paraben Free

Distributed by: GSK Consumer Healthcare, Warren, NJ 07059

For most recent product information, visit www.chapstick.com

Trademarks owned or licensed by GSK.

©2021 GSK or licensor

PRINCIPAL DISPLAY PANEL

BRAND LIP CARE
ChapStick®
SKIN PROTECTANT

Supreme

CLASSIC CHERRY

3 STICKS

NET WT 0.15 OZ

(4 g) EACH

000071831